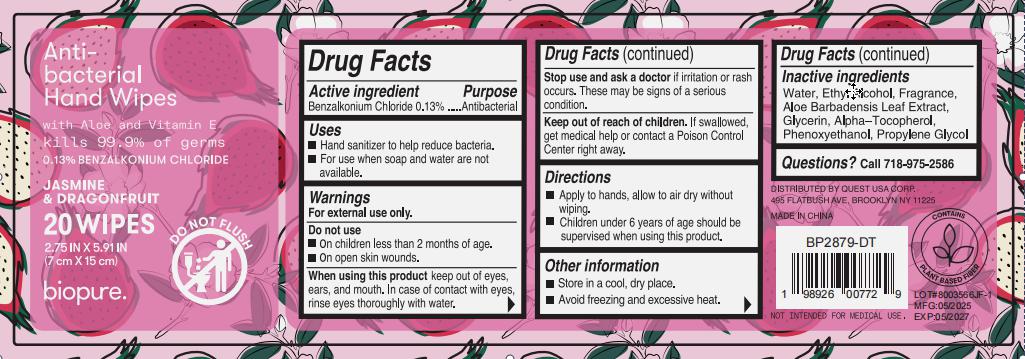 DRUG LABEL: BIOPURE20CT ANTI BACTERIAL HAND WIPES
NDC: 79794-114 | Form: CLOTH
Manufacturer: Zhejiang Furuisen Spunlaced Nonwovens Co., Ltd.
Category: otc | Type: HUMAN OTC DRUG LABEL
Date: 20250521

ACTIVE INGREDIENTS: BENZALKONIUM CHLORIDE 0.13 g/100 g
INACTIVE INGREDIENTS: ALCOHOL; PROPYLENE GLYCOL; GLYCERIN; PHENOXYETHANOL; WATER; ALPHA-TOCOPHEROL; ALOE VERA LEAF

79794-114-01

Active ingredient

Benzalkonium Chloride 0.13%

Purpose

Antibacterial

Uses

●Hand sanitizer to help reduce bacteria

●For use when soap and water are not available.

Warnings

For external use only.

Do not use

●in children less than 2 months old.

●on open skin wounds

When using this product

keep out of eyes, ears, and mouth. In case of contact with eyes, rinse eyes thoroughly with water.

Stop use and ask a doctor

if irritation or rash occurs.

These may be signs of a serious condition

Keep out of reach of children.

If swallowed. get medical help or contact a Poison Control Center right away.

Directions

●Apply to hands, allow to air dry without wiping.
●Children under 6 years of age should be supervised when using this product

Other information

●Store in a cool, dry place

●Avoid freezing and excessive heat

Inactive ingredients

Water, Glycerin, Phenoxyethanol, Propylene Glycol, Aloe Barbadensis Leaf Extract, Alpha-Tocopherol, Ethyl alcohol, Fragrance

Question?

Call 718-975-2586